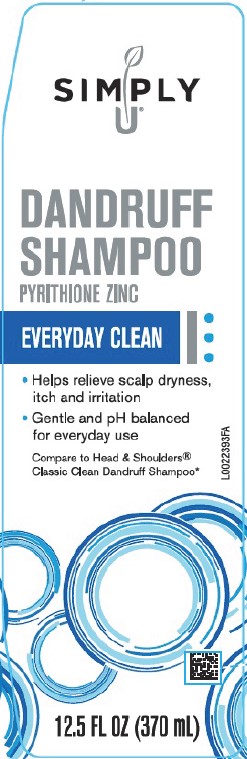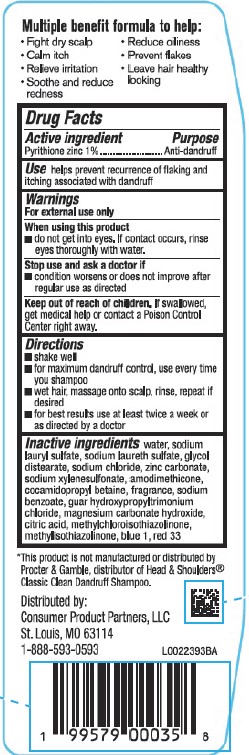 DRUG LABEL: Dandruff
NDC: 11344-153 | Form: SHAMPOO
Manufacturer: Consumer Product Partners, LLC
Category: otc | Type: HUMAN OTC DRUG LABEL
Date: 20250814

ACTIVE INGREDIENTS: PYRITHIONE ZINC 10 mg/1 mL
INACTIVE INGREDIENTS: WATER; SODIUM CHLORIDE; ZINC CARBONATE; METHYLISOTHIAZOLINONE; FD&C BLUE NO. 1; SODIUM XYLENESULFONATE; SODIUM LAURETH SULFATE; GLYCOL DISTEARATE; SODIUM LAURYL SULFATE; D&C RED NO. 33; COCAMIDOPROPYL BETAINE; METHYLCHLOROISOTHIAZOLINONE; CITRIC ACID MONOHYDRATE; GUAR HYDROXYPROPYLTRIMONIUM CHLORIDE (1.7 SUBSTITUENTS PER SACCHARIDE); AMODIMETHICONE (800 CST); SODIUM BENZOATE; MAGNESIUM CARBONATE HYDROXIDE

Simply U 153.008/153BD
Everyday Clean Dandruff Shampoo

Claims

Multiple benefit formula to help:

- Fight dry scalp
- Reduce oiliness
- Calm itch
- Prevent flakes
- Relieve irritation
- Leave hair healthy looking
- Soothe and reduce redness

Active ingredient

Pyrithione zinc 1%

Purpose

Anti-dandruff

Use

helps prevent recurrence of flaking and itching associated with dandruff

Warnings

For external use only

When using this product

- do not get into eyes. If contact occurs, rinse eyes thoroughly with water.

Stop use and ask a doctor if

- condition worsens or does not improve after regular use as directed

Keep out of reach of children.

If swallowed, get medical help or contact a Poison Control Center right away.

Directions

- shake well
- for maximum dandruff control, use every time you shampoo
- wet hair, massage onto scalp, rinse, repeat if desired
- for best results use at least twice a week or as directed by a doctor

Inactive ingredients

water, sodium lauryl sulfate, sodium laureth sulfate, glycol distearate, sodium chloride, zinc carbonate, sodium xylenesulfonate, amodimethicone, cocamidopropyl betaine, fragrance, sodium benzoate, guar hydroxypropyltrimonium chloride, magnesium carbonate hydroxide, citric acid, methylchloroisothiazolinone, methylisothiazolinone, blue 1, red 33

Disclaimer

*This product is not manufactured or distributed by Procter & Gamble, distributor of Head & Shoulders® Classic Clean Dandruff Shampoo.

Adverse Reaction

Distributed by: Consumer Product Partners, LLC

St. Louis, MO 63114

1-888-593-0593

Principal display panel

SIMPLY U®

DANDRUFF

SHAMPOO

PYRITHIONE ZINC

EVERYDAY CLEAN

- Helps relieve scalp dryness, itch and irritaion
- Gentle and pH balanced for everyday use

Compare to Head & Shoulders® Classic Clean Dandruff Shampoo*

12.5 FL OZ (370 mL)